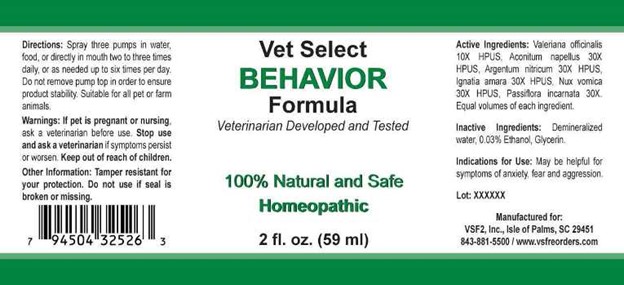 DRUG LABEL: Behavior
NDC: 86100-0005 | Form: LIQUID
Manufacturer: Vsf2, Inc.
Category: homeopathic | Type: OTC ANIMAL DRUG LABEL
Date: 20251110

ACTIVE INGREDIENTS: VALERIAN 10 [hp_X]/1 mL; ACONITUM NAPELLUS 30 [hp_X]/1 mL; SILVER NITRATE 30 [hp_X]/1 mL; STRYCHNOS IGNATII SEED 30 [hp_X]/1 mL; STRYCHNOS NUX-VOMICA SEED 30 [hp_X]/1 mL; PASSIFLORA INCARNATA FLOWERING TOP 30 [hp_X]/1 mL
INACTIVE INGREDIENTS: WATER; ALCOHOL

Drug Facts:

ACTIVE INGREDIENTS:

Valeriana Officinalis 10X HPUS, Aconitum Napellus 30X HPUS, Argentum Nitricum 30X HPUS, Ignatia Amara 30X HPUS, Nux Vomica 30X HPUS, Passiflora Incarnata 30X HPUS.

INDICATIONS FOR USE:

May be helpful for symptoms of anxiety, fear and aggresion.

WARNINGS:

If pet is pregnant or nursing, ask a veterinarian before use.

Stop use and ask a veterinarian if symptoms persist or worsen.

Keep out of reach of children.

Other Information: Tamper resistant for your protection. Do not use if seal is broken or missing.

KEEP OUT OF THE REACH OF CHILDREN:

Keep out of reach of children.

DIRECTIONS:

Spray three pumps in water, food, or directly in mouth two to three times daily, or as needed up to six times per day. Do not remove pump top in order to ensure product stability. Suitable for all pet or farm animals.

INDICATIONS FOR USE:

May be helpful for symptoms of anxiety, fear and aggresion.

INACTIVE INGREDIENTS:

Demineralized water, Ethanol 20%.

QUESTIONS:

Manufactured for:

VSF2, Inc., Isle of Palms, SC 29451

843-881-5500 / www.vsfreorders.com

PACKAGE LABEL DISPLAY:

Vet Select

BEHAVIOR

Formula

Veterinarian Developed and Tested

100% Natural and Safe

Homeopathic

2 fl. oz. (59 ml)